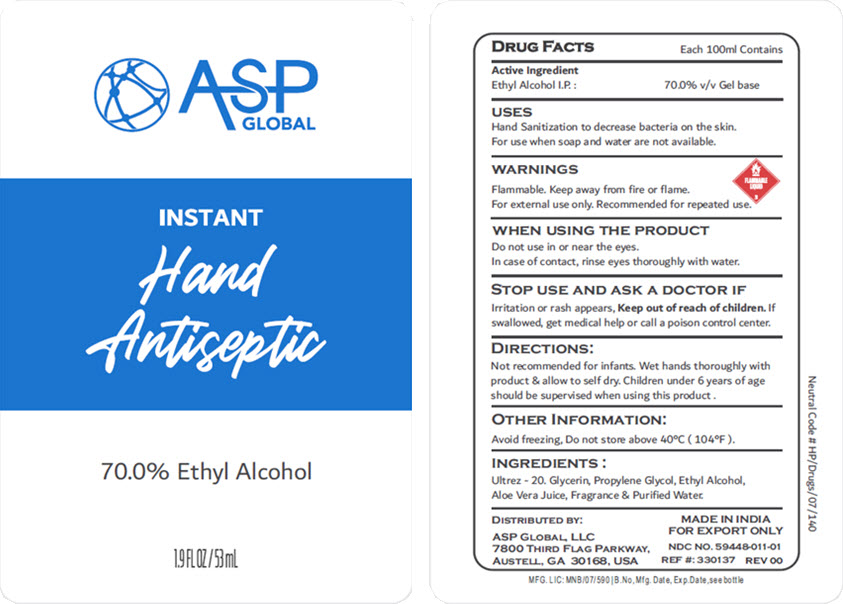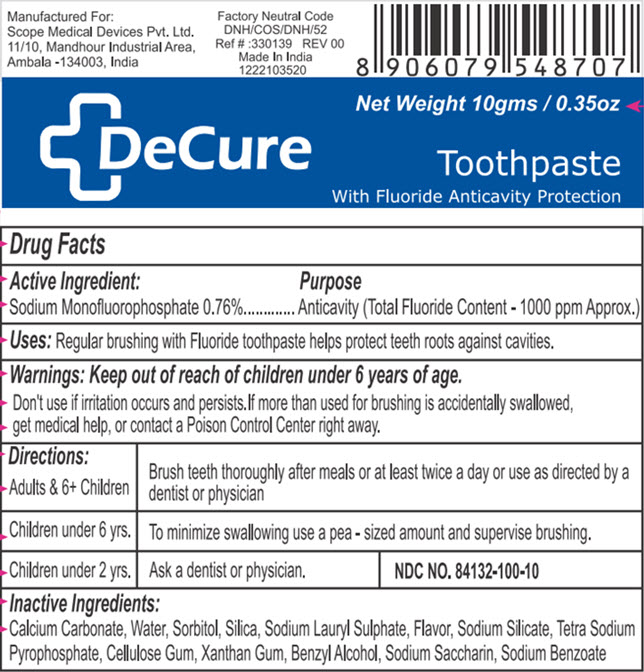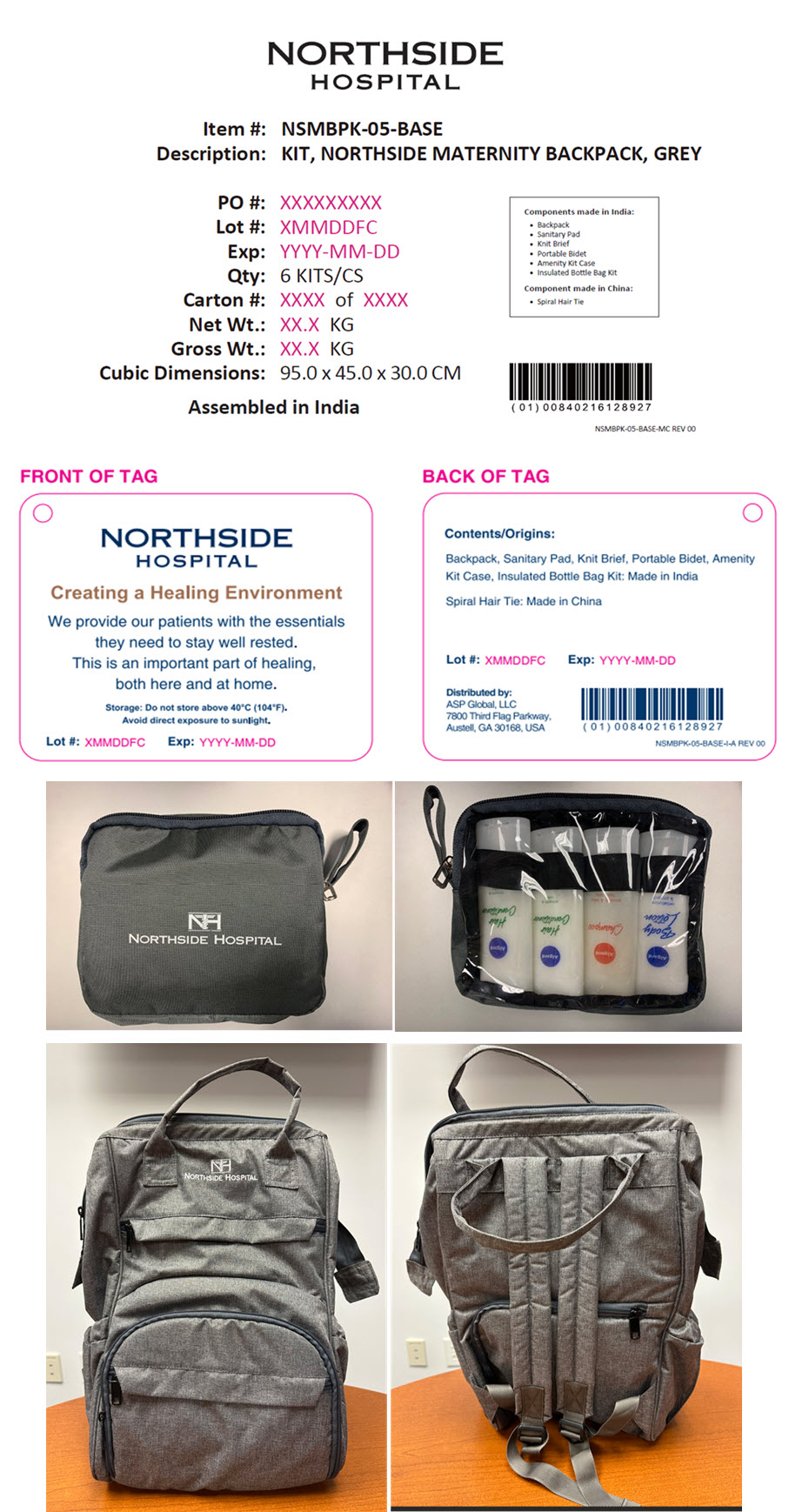 DRUG LABEL: Northside Hospital Maternity Backpack-BASE
NDC: 59448-215 | Form: KIT | Route: TOPICAL
Manufacturer: ASP Global, LLc
Category: otc | Type: HUMAN OTC DRUG LABEL
Date: 20251022

ACTIVE INGREDIENTS: ALCOHOL 70 mL/100 mL; SODIUM MONOFLUOROPHOSPHATE 7.6 mg/1 g
INACTIVE INGREDIENTS: Water; Aloe Vera Leaf; Glycerin; Propylene Glycol; Acrylates/C10-30 Alkyl Acrylate Crosspolymer (60000 Mpa.S At 0.5%); Fragrance 13576; Calcium Carbonate; Water; Sorbitol; Sodium Lauryl Sulfate; Sodium Pyrophosphate; Saccharin Sodium; Silicon Dioxide; Sodium Silicate; Carboxymethylcellulose Sodium, Unspecified; Xanthan Gum; Benzyl Alcohol; Sodium Benzoate; Methyl Salicylate

Northside Hospital Maternity Backpack-BASE

ETHYL ALCOHOL GEL

DRUG FACTS

Active Ingredient

Ethyl Alcohol I.P.

PURPOSE

70.0% v/v Gel base

USES

Hand Sanitization to decrease bacteria on the skin.

For use when soap and water are not available.

WARNINGS

Flammable. Keep away from fire or flame.

For external use only. Recommended for repeated use.

WHEN USING THE PRODUCT

Do not use in or near the eyes.

In case of contact, rinse eyes thoroughly with water.

STOP USE AND ASK A DOCTOR IF

Irritation or rash appears,

Keep out of reach of children. If swallowed, get medical help or call a poison control center.

DIRECTIONS

Not recommended for infants. Wet hands thoroughly with product & allow to self dry. Children under 6 years of age should be supervised when using this product .

OTHER INFORMATION

Avoid freezing, Do not store above 40°C (104°F).

INGREDIENTS

Ultrez - 20. Glycerin, Propylene Glycol, Ethyl Alcohol, Aloe Vera Juice, Fragrance & Purified Water.

DISTRIBUTED BY:

ASP GLOBAL, LLC
7800 THIRD FLAG PARKWAY,
AUSTELL, GA 30168, USA

DeCure Toothpaste

Drug Facts

Active Ingredient

Sodium Monofluorophosphate 0.76%

Purpose

Anticavity (Total Fluoride Content - 1000 ppm Approx.)

Uses

Regular brushing with Fluoride toothpaste helps protect teeth roots against cavities.

Warnings

Keep out of reach of children under 6 years of age.

DO NOT USE

Don't use if irritation occurs and persists. If more than used for brushing is accidentally swallowed, get medical help, or contact a Poison Control Center right away.

Directions

Adults & 6+ Children | Brush teeth thoroughly after meals or at least twice a day or use as directed by a dentist or physician
Children under 6 yrs. | To minimize swallowing use a pea - sized amount and supervise brushing.
Children under 2 yrs. | Ask a dentist or physician. | NDC NO. 84132-100-10

Inactive Ingredients

Calcium Carbonate, Water, Sorbitol, Silica, Sodium Lauryl Sulphate, Flavor, Sodium Silicate, Tetra Sodium Pyrophosphate, Cellulose Gum, Xanthan Gum, Benzyl Alcohol, Sodium Saccharin, Sodium Benzoate

PRINCIPAL DISPLAY PANEL - 53 mL Bottle Label

ASP
GLOBAL

INSTANT
Hand
Antiseptic

70.0% Ethyl Alcohol

1.9 FL OZ/53 mL

PRINCIPAL DISPLAY PANEL - 10 gm Tube Label

Net Weight 10gms / 0.35oz

DeCure

Toothpaste
With Fluoride Anticavity Protection

PRINCIPAL DISPLAY PANEL - Kit Label

NORTHSIDE
HOSPITAL

Item #: NSMBPK-05-BASE

Description: KIT, NORTHSIDE MATERNITY BACKPACK, GREY

PO #: XXXXXXXXX

Lot #: XMMDDFC

Exp: YYYY-MM-DD

Qty: 6 KITS/CS

Carton #: XXXX of XXXX

Net Wt.: XX.X KG

Gross Wt.: XX.X KG

Cubic Dimensions: 95.0 x 45.0 x 30.0 CM

Assembled in India

Components made in India:

- Backpack
- Sanitary Pad
- Knit Brief
- Portable Bidet
- Amenity Kit Case
- Insulated Bottle Bag Kit

Component made in China:

- Spiral Hair Tie

NSMBPK-05-BASE-MC REV 00

NORTHSIDE
HOSPITAL

Creating a Healing Environment

We provide our patients with the essentials
they need to stay well rested.
This is an important part of healing,
both here and at home.

Storage: Do not store above 40°C (104°F).
Avoid direct exposure to sunlight.

Lot #: XMMDDFC

Exp: YYYY-MM-DD

Contents/Origins:

Backpack, Sanitary Pad, Knit Brief, Portable Bidet, Amenity
Kit Case, Insulated Bottle Bag Kit: Made in India

Spiral Hair Tie: Made in China

Lot #: XMMDDFC

Exp: YYYY-MM-DD

Distributed by:
ASP Global, LLC
7800 Third Flag Parkway,
Austell, GA 30168, USA

NSMBPK-05-BASE-I-A REV 00

NORTHSIDE HOSPITAL

NORTHSIDE HOSPITAL